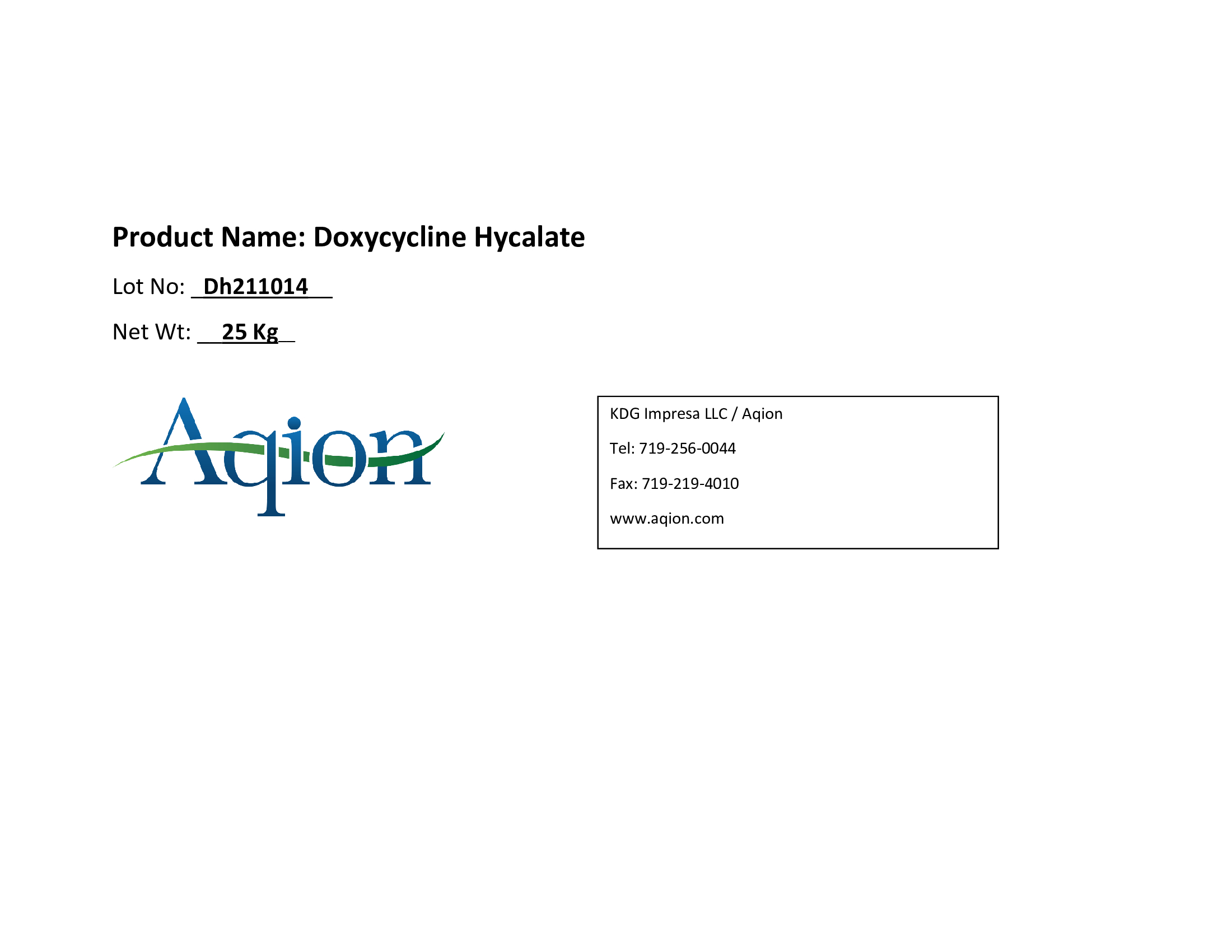 DRUG LABEL: Doxycycline Hycalate
NDC: 43457-541 | Form: POWDER
Manufacturer: KDG Impresa LLC, Aqion
Category: other | Type: BULK INGREDIENT - ANIMAL DRUG
Date: 20220223

ACTIVE INGREDIENTS: DOXYCYCLINE HYCLATE 1 kg/1 kg

Doxycycline Hycalate